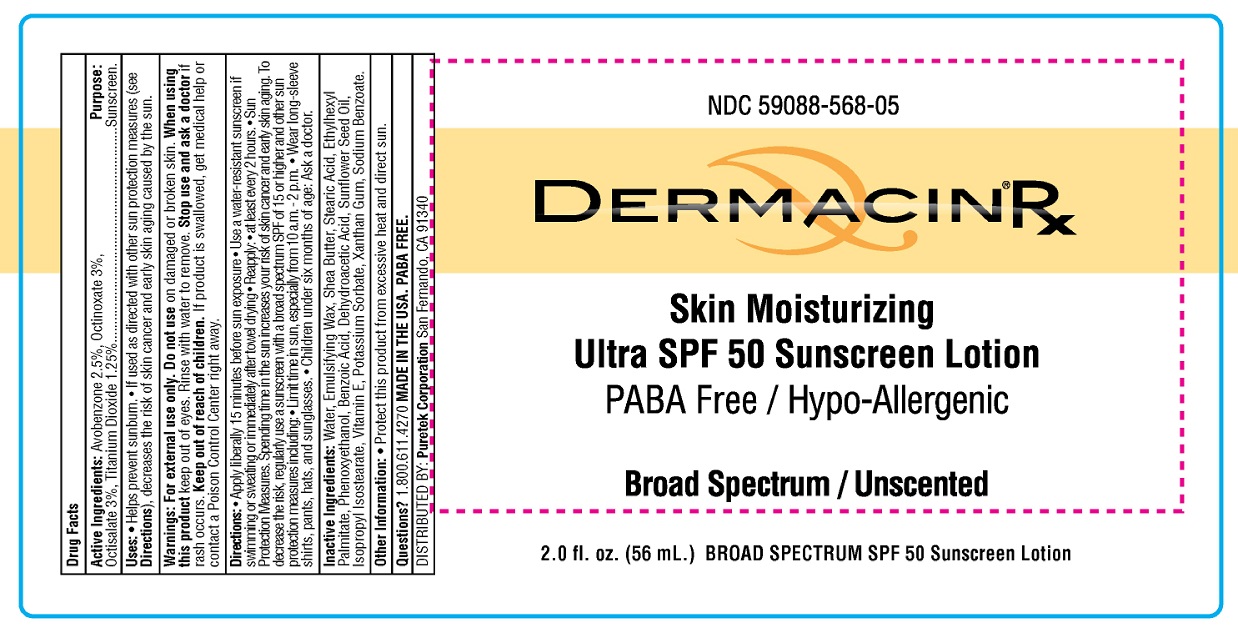 DRUG LABEL: DermacinRx Skin Moisturizing Ultra SPF 50 Sunscreen
NDC: 59088-568 | Form: LOTION
Manufacturer: PureTek Corporation
Category: otc | Type: HUMAN OTC DRUG LABEL
Date: 20241002

ACTIVE INGREDIENTS: AVOBENZONE 25 mg/1 mL; OCTINOXATE 30 mg/1 mL; OCTISALATE 30 mg/1 mL; TITANIUM DIOXIDE 12.5 mg/1 mL
INACTIVE INGREDIENTS: WATER; POLAWAX POLYSORBATE; SHEA BUTTER; STEARIC ACID; ETHYLHEXYL PALMITATE; PHENOXYETHANOL; BENZOIC ACID; DEHYDROACETIC ACID; SUNFLOWER OIL; ISOPROPYL ISOSTEARATE; .ALPHA.-TOCOPHEROL; POTASSIUM SORBATE; XANTHAN GUM; SODIUM BENZOATE

Dermacin®Rx Skin Moisturizing Ultra SPF 50 Sunscreen Lotion
(avobenzone, octinoxate, octisalate, titanium dioxide)

Active ingredients (% w/w)

Avobenzone 2.5%

Octinoxate 3%

Octisalate 3%

Titanium Dioxide 1.25%

Purposes

Sunscreen (Avobenzone 2.5%)
Sunscreen (Octinoxate 3%)
Sunscreen (Octisalate 3%)
Sunscreen (Titanium Dioxide 1.25%)

Uses

■ Helps prevent sunburn.

■ If used as a directed with other sun protection measures (see Directions), decreases the risk of cancer and early skin aging caused by the sun.

Warnings

For external use only

Do not use

■ on damaged or broken skin

When using this product

■ keep out of eyes

■ Rinse with water to remove

Stop use and ask a doctor if

■ rash occurs

Keep out of reach of children.

If product is swallowed, get medical help or contact a Poison Control Center right away.

Directions

■ Apply liberally 15 minutes before sun exposure ■ Use a water-resistant sunscreen if swimming or sweating or immediately after towel drying
■ Reaply: ■ at least every 2 hours. ■ Sun Protection Measures. Spending time in the sun increases your risk of skin cancer and early skin aging. To decrease the risk, regularly use a sunscreen with a broad spectrum SPF of 15 or higher and other sun protection measures including: ■ Limit time in the sun, especially from 10 a.m. - 2 p.m. ■ Wear long-sleeve shirts, pants, hats, and sunglasses. ■ Children under six months of age: Ask a doctor.

Inactive ingredients

Water, Emulsifying Wax, Shea butter, Stearic Acid, Ethylhexyl Palmitate, Phenoxyethanol, Benzoic Acid, Dehydroacetic Acid, Sunflower Seed Oil, Isopropyl Isostearate, Vitamin E, Potassium Sorbate, Xanthan Gum, Sodium Benzoate.

Other information

■ Protect this product from excessive heat and direct sun

Questions?

1.800.611.4270

Dermacin®Rx Skin Moisturizing Ultra SPF 50 Sunscreen Lotion (Label)

DISTRIBUTED BY:

PureTek Corporation
San Fernando, CA 91340